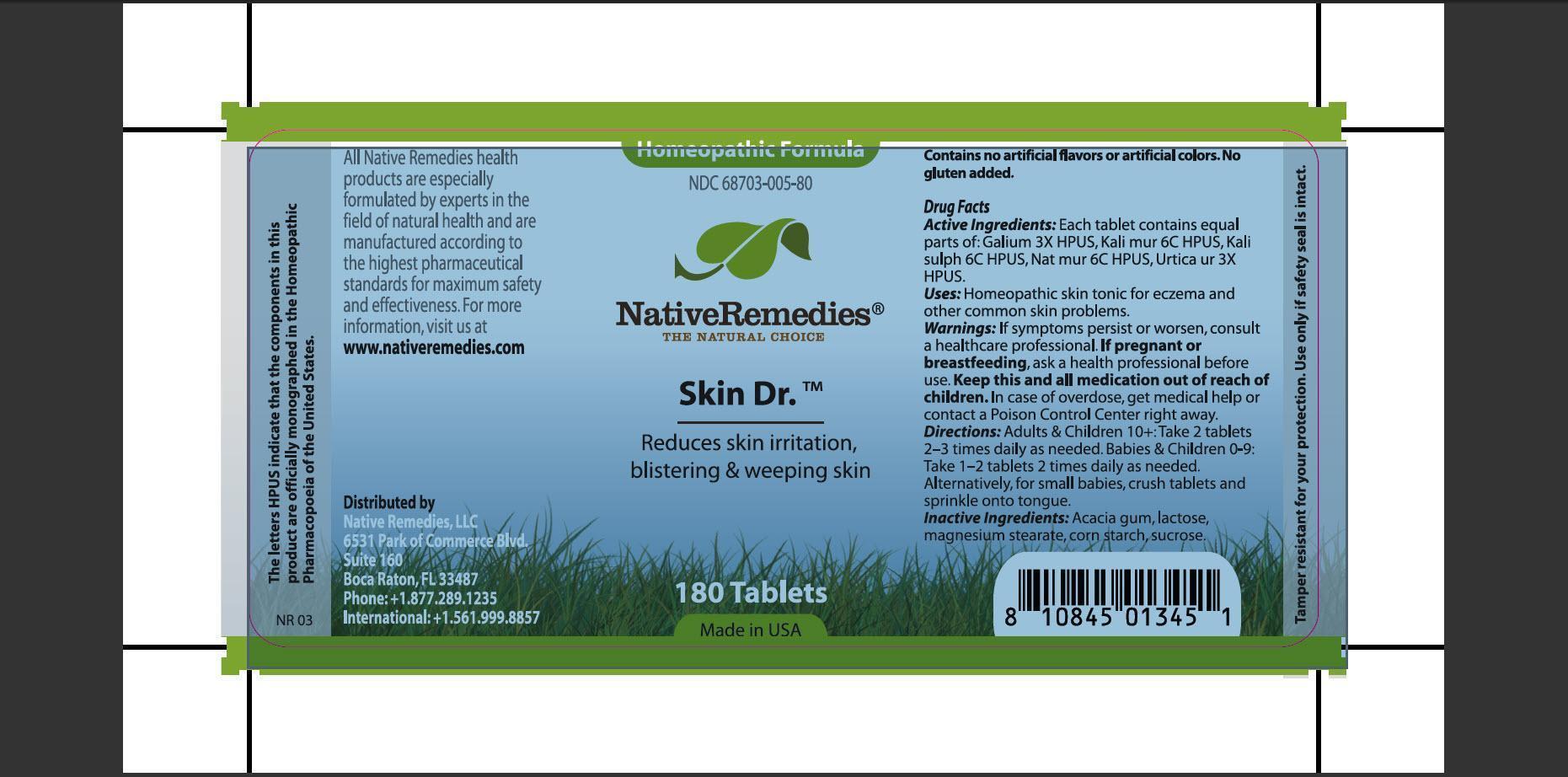 DRUG LABEL: Skin Dr
NDC: 68703-005 | Form: TABLET
Manufacturer: Native Remedies LLC
Category: homeopathic | Type: HUMAN OTC DRUG LABEL
Date: 20130115

ACTIVE INGREDIENTS: GALIUM APARINE 3 [hp_X]/1 1; POTASSIUM CHLORIDE 6 [hp_C]/1 1; POTASSIUM SULFATE 6 [hp_C]/1 1; SODIUM CHLORIDE 6 [hp_C]/1 1; URTICA URENS 6 [hp_C]/1 1
INACTIVE INGREDIENTS: ACACIA; LACTOSE; MAGNESIUM STEARATE; STARCH, CORN; SUCROSE

SKIN DR

PURPOSE

Reduces skin irritation, blistering and weeping skin

ACTIVE INGREDIENT

Active Ingredients: Each tablet contains equal parts of: Galium 3X HPUS, Kali mur 6C HPUS, Kali sulph 6C HPUS, Nat mur 6C HPUS, Urtica ur 3X HPUS.

INDICATIONS AND USAGE

Uses: Homeopathic skin tonic for eczema and other common skin problems.

WARNINGS

Warnings: If symptoms persist or worsen, consult a healthcare professional.

PREGNANCY OR BREAST FEEDING

If pregnant or breastfeeding, ask a health professional before use.

KEEP OUT OF REACH OF CHILDREN

Keep this and all medication out of reach of children.

OVERDOSAGE

In case of overdose, get medical help or contact a Poison Control center right away.

DOSAGE AND ADMINISTRATION

Directions: Adults and Children 10+: Take 2 tablets 2-3 times daily as needed. Babies and Children 0-9: Take 1-2 tablets 2 times daily as needed. Alternatively, for small babies, crush tablets and sprinkle onto tongue.

INACTIVE INGREDIENT

Inactive Ingredients: Acacia gum, lactose, magnesium stearate, corn starch, sucrose.

PATIENT COUNSELING INFORMATION

The letters HPUS indicate that the components in this product are officially monographed in the Homeopathic Pharmacopoeia of the United States.

All Native Remedies health products are especially formulated by experts in the field of natural health and are manufactured according to the highest pharmaceutical standards for maximum safety and effectiveness. For more information, visit us at www.nativeremedies.com

Distributed by
Native Remedies, LLC
6531 Park of Commerce Blvd.
Suite 160
Boca Raton, FL 33487
Phone: +1.877.289.1235
International: +1.561.999.8857

Contains no artificial flavors or artificial colors. No gluten added.

STORAGE AND HANDLING

Tamper resistant for your protection. Use only if safety seal is intact.